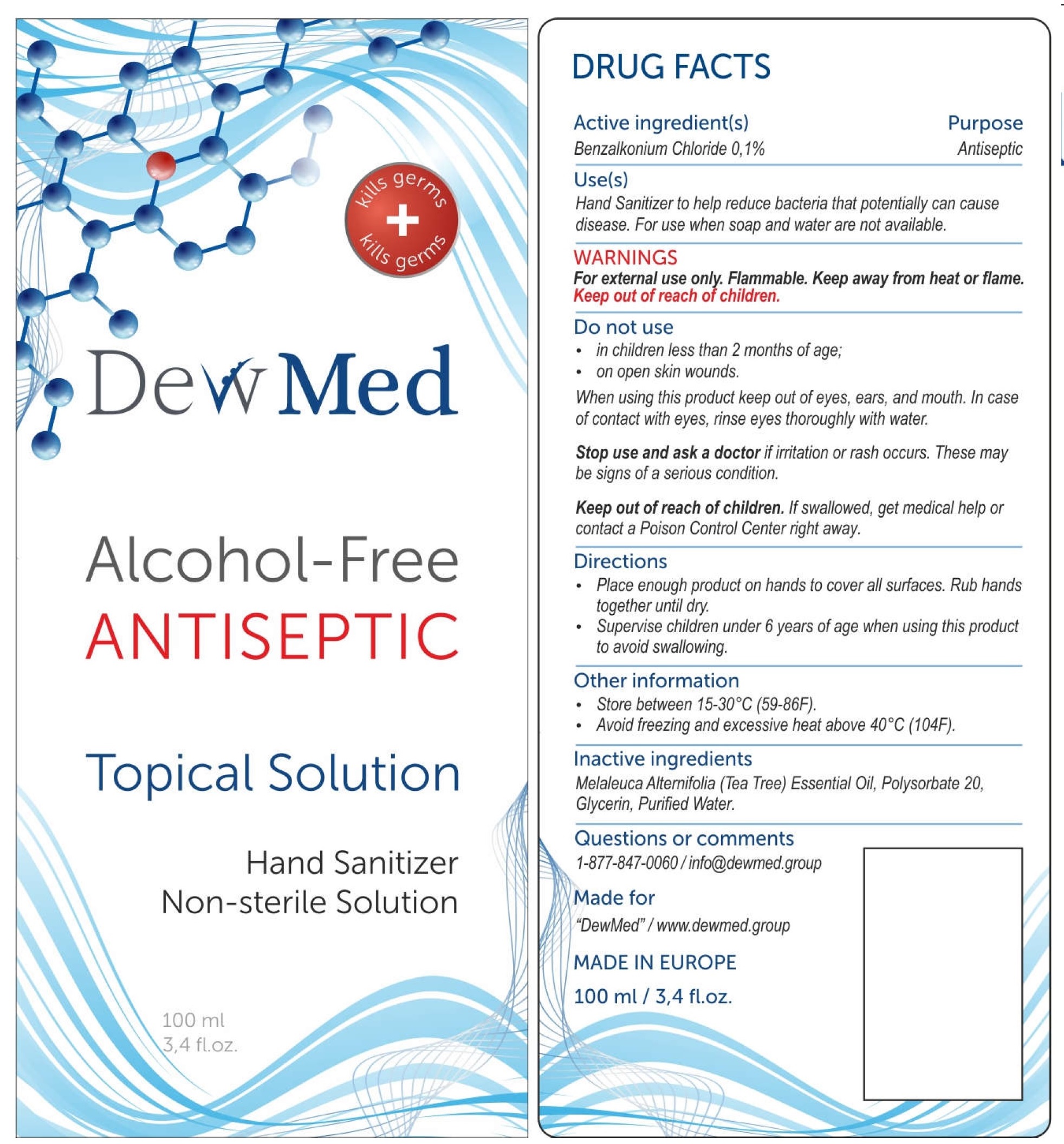 DRUG LABEL: DewMed Alcohol Free Antiseptic Topical Solution Hand Sanitizer
NDC: 80065-002 | Form: GEL
Manufacturer: DewMed LLC
Category: otc | Type: HUMAN OTC DRUG LABEL
Date: 20200917

ACTIVE INGREDIENTS: BENZALKONIUM CHLORIDE 1 mg/1 mL
INACTIVE INGREDIENTS: TEA TREE OIL; POLYSORBATE 20; GLYCERIN; WATER

DewMed Alcohol Free Antiseptic Topical Solution Hand Sanitizer

Active ingredient[s]

Benzalkonium Chloride 0.1%

Purpose

Antiseptic

Use[s]

Hand Sanitizer to help reduce bacteria that potentially can cause disease. For use when soap and water are not available.

WARNINGS

For external use only. Keep away from heat or flame.

Do not use

- in children less than 2 months of age;
- on open skin wounds

When using this product

keep out of eyes, ears, and mouth. In case of contact with eyes, rinse eyes thoroughly with water.

Stop use and ask a doctor if

if irritation or rash occurs. These may be signs of a serious condition.

Keep out of reach of children.

If swallowed, get medical help or contact a Poison Control Center right away.

Directions

- Place enough product on hands to cover all surfaces. Rub hands together until dry.
- Supervise children under 6 years of age when using this product to avoid swallowing.

Other information

- Store between 15-30°C (59-86F).
- Avoid freezing and excessive heat above 40°C (104F).

Inactive ingredients

Melaleuca Alternifolia (Tea Tree) Essential Oil, Polysorbate 20, Glycerin, Purified Water.

Questions or comments

1-877-847-0060 / info@dewmed.group